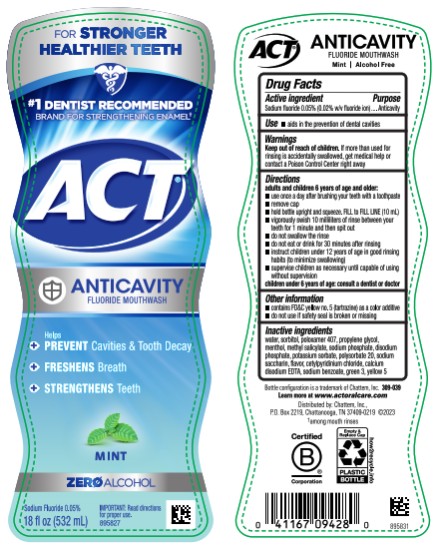 DRUG LABEL: ACT Anticavity Fluoride Mint
NDC: 41167-0942 | Form: RINSE
Manufacturer: Chattem, Inc.
Category: otc | Type: HUMAN OTC DRUG LABEL
Date: 20260112

ACTIVE INGREDIENTS: SODIUM FLUORIDE 0.2 mg/1 mL
INACTIVE INGREDIENTS: WATER; SORBITOL; POLOXAMER 407; PROPYLENE GLYCOL; MENTHOL; METHYL SALICYLATE; SODIUM PHOSPHATE; SODIUM PHOSPHATE, DIBASIC, ANHYDROUS; POTASSIUM SORBATE; POLYSORBATE 20; SACCHARIN SODIUM; MINT; CETYLPYRIDINIUM CHLORIDE; EDETATE CALCIUM DISODIUM ANHYDROUS; SODIUM BENZOATE; FD&C GREEN NO. 3; FD&C YELLOW NO. 5

ACT Anticavity Fluoride Rinse Mint

Drug Facts

Active ingredient

Sodium fluoride 0.05% (0.02% w/v fluoride ion)

Purpose

Anticavity

Use

- aids in the prevention of dental cavities

Warnings

Keep out of reach of children.

If more than used for rinsing is accidentally swallowed, get medical help or contact a Poison Control Center right away.

Directions

adults and children 6 years of age and older:

- use once a day after brushing your teeth with a toothpaste
- remove cap
- hold bottle upright and squeeze. Fill to FILL LINE (10 mL)
- vigorously swish 10 milliliters of rinse between your teeth for 1 minute and then spit out
- do not swallow the rinse
- do not eat or drink for 30 minutes after rinsing
- instruct children under 12 years of age in good rinsing habits (to minimize swallowing)
- supervise children as necessary until capable of using without supervision

children under 6 years of age: consult a dentist or doctor

Other information

- contains FD&C yellow no. 5 (tartrazine) as a color additive
- do not use if safety seal is broken or missing

Inactive ingredients

water, sorbitol, poloxamer 407, propylene glycol, menthol, methyl salicylate, sodium phosphate, disodium phosphate, potassium sorbate, polysorbate 20, sodium saccharin, flavor, cetylpyridinium chloride, calcium disodium EDTA, sodium benzoate, green 3, yellow 5

Learn more at www.ACTFLUORIDE.com

PRINCIPAL DISPLAY PANEL

ZERO ALCOHOL
#1 DENTIST RECOMMENDED
FLUORIDE BRAND
ACT
1X Daily
ANTICAVITY
FLUORIDE MOUTHWASH
MINT
18 fl oz (532 mL)